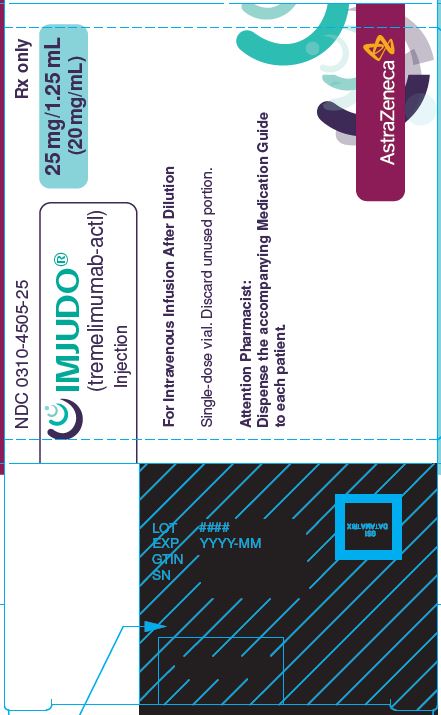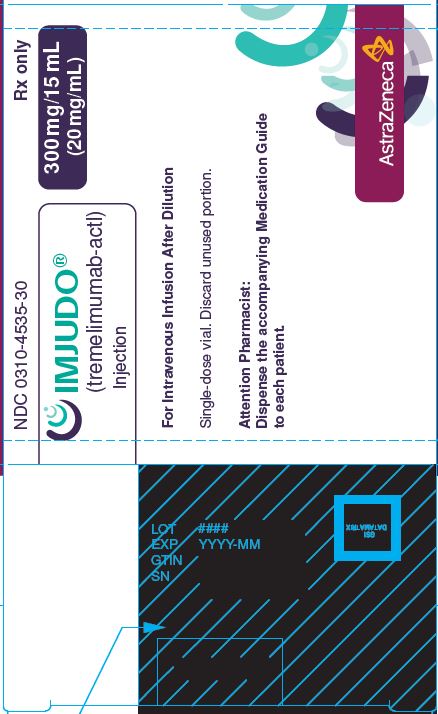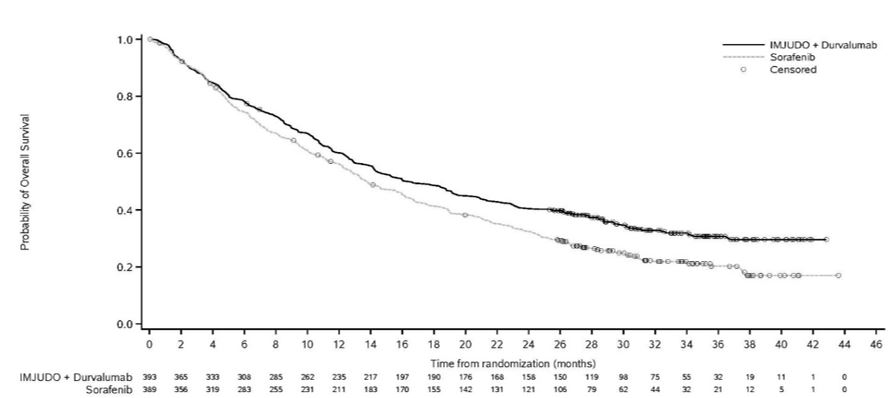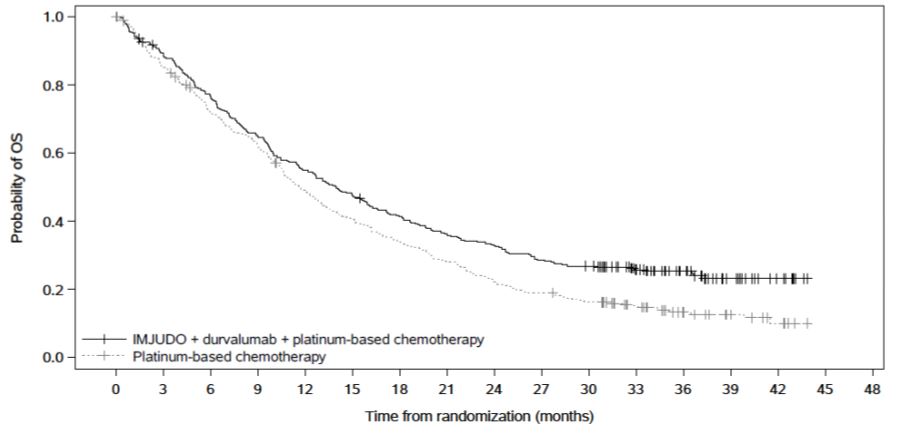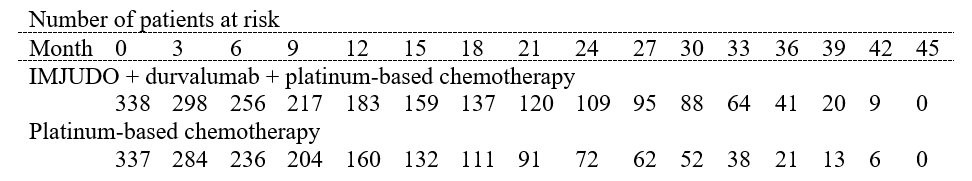 DRUG LABEL: IMJUDO
NDC: 0310-4505 | Form: INJECTION, SOLUTION
Manufacturer: AstraZeneca Pharmaceuticals LP
Category: prescription | Type: HUMAN PRESCRIPTION DRUG LABEL
Date: 20240724

ACTIVE INGREDIENTS: TREMELIMUMAB 25 mg/1.25 mL
INACTIVE INGREDIENTS: EDETATE DISODIUM 0.1 mg/1.25 mL; HISTIDINE 1 mg/1.25 mL; HISTIDINE MONOHYDROCHLORIDE MONOHYDRATE 4 mg/1.25 mL; POLYSORBATE 80 0.3 mg/1.25 mL; TREHALOSE 105 mg/1.25 mL; WATER 1.2 g/1.25 mL

HIGHLIGHTS OF PRESCRIBING INFORMATION

These highlights do not include all the information needed to use IMJUDO safely and effectively. See full prescribing information for IMJUDO.
IMJUDO® (tremelimumab-actl) injection, for intravenous use
Initial U.S. Approval: 2022

1 INDICATIONS AND USAGE

IMJUDO is a cytotoxic T-lymphocyte-associated antigen 4 (CTLA-4) blocking antibody indicated:

- in combination with durvalumab, for the treatment of adult patients with unresectable hepatocellular carcinoma (uHCC). (1.1)
- in combination with durvalumab and platinum-based chemotherapy for the treatment of adult patients with metastatic non-small cell lung cancer (NSCLC) with no sensitizing epidermal growth factor receptor (EGFR) mutation or anaplastic lymphoma kinase (ALK) genomic tumor aberrations. (1.2)

2 DOSAGE AND ADMINISTRATION

- Administer IMJUDO as an intravenous infusion over 60 minutes after dilution. (2.3)
- uHCC:

Weight 30 kg and more: IMJUDO 300 mg as a single dose in combination with durvalumab 1,500 mg at Cycle 1/Day 1, followed by durvalumab as a single agent every 4 weeks (2.1)

Weight less than 30 kg: IMJUDO 4 mg/kg as a single dose in combination with durvalumab 20 mg/kg at Cycle 1/Day 1, followed by durvalumab as a single agent every 4 weeks (2.1)

- Metastatic NSCLC:

Weight 30 kg and more: 75 mg every 3 weeks in combination with durvalumab 1,500 mg and platinum-based chemotherapy for 4 cycles, and then administer durvalumab 1,500 mg every 4 weeks as a single agent with histology-based pemetrexed therapy every 4 weeks, and a fifth dose of IMJUDO 75 mg in combination with durvalumab dose 6 at week 16 (2.1)

Weight less than 30 kg: 1 mg/kg every 3 weeks in combination with durvalumab 20 mg/kg and platinum-based chemotherapy for 4 cycles, and then administer durvalumab 20 mg/kg every 4 weeks as a single agent with histology-based pemetrexed therapy every 4 weeks, and a fifth dose of IMJUDO 1 mg/kg in combination with durvalumab dose 6 at week 16 (2.1)

- See full Prescribing Information for preparation and administration instructions and dosage modifications for adverse reactions.

3 DOSAGE FORMS AND STRENGTHS

- Injection: 25 mg/1.25 mL (20 mg/mL) solution in a single-dose vial. (3)
- Injection: 300 mg/15 mL (20 mg/mL) solution in a single-dose vial. (3)

4 CONTRAINDICATIONS

None. (4)

5 WARNINGS AND PRECAUTIONS

- Immune-Mediated Adverse Reactions (5.1)

Immune-mediated adverse reactions, which may be severe or fatal, can occur in any organ system or tissue, including the following: immune-mediated pneumonitis, immune-mediated colitis, immune-mediated hepatitis, immune-mediated endocrinopathies, immune-mediated nephritis with renal dysfunction, immune-mediated dermatologic adverse reactions and immune-mediated pancreatitis.

    - Monitor for early identification and management. Evaluate liver enzymes, creatinine, adrenocorticotropic hormone level and thyroid function at baseline and before each dose.
    - Withhold or permanently discontinue based on severity and type of reaction.
- Infusion-Related Reactions: Interrupt, slow the rate of infusion, or permanently discontinue treatment based on the severity of the reaction. (5.2)
- Embryo-Fetal Toxicity: Can cause fetal harm. Advise females of reproductive potential of the potential risk to a fetus and use of effective contraception. (5.3, 8.1, 8.3)

6 ADVERSE REACTIONS

Most common adverse reactions (≥ 20%) of patients with uHCC are rash, diarrhea, fatigue, pruritus, musculoskeletal pain, and abdominal pain. Most common laboratory abnormalities (≥ 40%) of patients with uHCC are AST increased, ALT increased, hemoglobin decreased, sodium decreased, bilirubin increased, alkaline phosphatase increased, and lymphocytes decreased. (6.1)

Most common adverse reactions (≥ 20%) of patients with metastatic NSCLC were nausea, fatigue, musculoskeletal pain, decreased appetite, rash, and diarrhea. (6.1)

To report SUSPECTED ADVERSE REACTIONS, contact AstraZeneca at 1-800-236-9933 or FDA at 1-800-FDA-1088 or www.fda.gov/medwatch.

8 USE IN SPECIFIC POPULATIONS

Lactation: Advise not to breastfeed. (8.2)

FULL PRESCRIBING INFORMATION

1 INDICATIONS AND USAGE

1.1 Hepatocellular Carcinoma

IMJUDO, in combination with durvalumab, is indicated for the treatment of adult patients with unresectable hepatocellular carcinoma (uHCC).

1.2 Non-Small Cell Lung Cancer (NSCLC)

IMJUDO, in combination with durvalumab and platinum-based chemotherapy, is indicated for the treatment of adult patients with metastatic NSCLC with no sensitizing epidermal growth factor receptor (EGFR) mutations or anaplastic lymphoma kinase (ALK) genomic tumor aberrations.

2 DOSAGE AND ADMINISTRATION

2.1 Recommended Dosage

The recommended dosages of IMJUDO are presented in Tables 1, 2 and 3.

Administer IMJUDO as an intravenous infusion after dilution as recommended [see Dosage and Administration (2.3)].

IMJUDO in Combination with Durvalumab

Table 1. Recommended dosage of IMJUDO
Indication | Recommended IMJUDO Dosage | Duration of Therapy
uHCC | Patients with a body weight of 30 kg and more:; - A single dose of IMJUDO [Administer IMJUDO prior to durvalumab on the same day.] 300 mg followed by durvalumab [Refer to the Prescribing Information for durvalumab dosing information.] 1,500 mg at Day 1 of Cycle 1; - Continue durvalumab 1,500 mg as a single agent every 4 weeks; Patients with a body weight of less than 30 kg:; - A single dose of IMJUDO 4 mg/kg followed by durvalumab 20 mg/kg at Day 1 of Cycle 1; - Continue durvalumab 20 mg/kg as a single agent every 4 weeks | After Cycle 1 of combination therapy, administer durvalumab as a single agent every 4 weeks until disease progression or unacceptable toxicity

IMJUDO in Combination with Durvalumab and Platinum-Based Chemotherapy

The recommended dosage schedule and regimens for IMJUDO for the treatment of metastatic non-small cell lung cancer (NSCLC) are provided in Tables 2 and 3.

Weigh patients prior to each infusion.

Calculate the appropriate dose using Table 3 below based on the patient’s weight and tumor histology.

Table 2: Recommended Dosage Schedule
 | Week [continue durvalumab until disease progression or intolerable toxicity.] , [dosing interval change from every 3 weeks to every 4 weeks starting at cycle 5.]
 | 0 | 1 | 2 | 3 | 4 | 5 | 6 | 7 | 8 | 9 | 10 | 11 | 12 | 13 | 14 | 15 | 16 | 17 | 18 | 19 | 20 | 21 | 22 | 23 | 24
Cycle: | 1 |  |  | 2 |  |  | 3 |  |  | 4 |  |  | 5 |  |  |  | 6 |  |  |  | 7 |  |  |  | 8
IMJUDO [intravenous infusion over 60 minutes [see Dosage and Administration (2.3)].] , [if patients receive fewer than 4 cycles of platinum-based chemotherapy, the remaining cycles of IMJUDO (up to a total of 5) should be given after the platinum-based chemotherapy phase, in combination with durvalumab, every 4 weeks.] | X |  |  | X |  |  | X |  |  | X |  |  |  |  |  |  | X
Durvalumab, | X |  |  | X |  |  | X |  |  | X |  |  | X |  |  |  | X |  |  |  | X |  |  |  | X
Chemotherapy | X |  |  | X |  |  | X |  |  | X |  |  | X [optional pemetrexed therapy from week 12 until disease progression or intolerable toxicity for patients with non-squamous disease who received treatment with pemetrexed and carboplatin/cisplatin.] |  |  |  | X |  |  |  | X |  |  |  | X

Table 3: Recommended Regimen and Dosage
Tumor Histology | Patient Weight | IMJUDO; Dosage | Durvalumab [Refer to the Prescribing Information for dosing information.]; Dosage | Platinum-based; Chemotherapy Regimen
Non-Squamous | ≥ 30 kg | 75 mg | 1,500 mg | - carboplatin & nab-paclitaxel; OR; - carboplatin or cisplatin & pemetrexed
Non-Squamous | < 30 kg | 1 mg/kg | 20 mg/kg | - carboplatin & nab-paclitaxel; OR; - carboplatin or cisplatin & pemetrexed
Squamous | ≥ 30 kg | 75 mg | 1,500 mg | - carboplatin & nab-paclitaxel; OR; - carboplatin or cisplatin & gemcitabine
Squamous | < 30 kg | 1 mg/kg | 20 mg/kg | - carboplatin & nab-paclitaxel; OR; - carboplatin or cisplatin & gemcitabine

2.2 Dosage Modifications for Adverse Reactions

No dose reduction for treatment is recommended. In general, withhold treatment regimen for severe (Grade 3) immune-mediated adverse reactions. Permanently discontinue treatment regimen for life-threatening (Grade 4) immune-mediated adverse reactions, recurrent severe (Grade 3) immune-mediated reactions that require systemic immunosuppressive treatment, or an inability to reduce corticosteroid dose to 10 mg or less of prednisone or equivalent per day within 12 weeks of initiating corticosteroids.

Recommended treatment modifications are presented in Table 4.

Table 4. Recommended Dosage Modifications for Adverse Reactions
Adverse Reaction | Severity [Based on National Cancer Institute Common Terminology Criteria for Adverse Events, version 4.03.] | Dosage Modification
Immune-Mediated Adverse Reactions [see Warnings and Precautions (5.1)]
Pneumonitis | Grade 2 | Withhold [Resume in patients with complete or partial resolution (Grade 0 to 1) after corticosteroid taper. Permanently discontinue if no complete or partial resolution within 12 weeks of initiating steroids or an inability to reduce corticosteroid dose to 10 mg of prednisone or less per day (or equivalent) within 12 weeks of initiating corticosteroids.]
Pneumonitis | Grade 3 or 4 | Permanently discontinue
Colitis | Grade 2 | Withhold
Colitis | Grade 3 or 4 | Permanently discontinue
Intestinal perforation | Any grade | Permanently discontinue
Hepatitis with no tumor involvement of the liver | ALT or AST increases to more than 3 and up to 8 times the ULN; or; total bilirubin increases to more than 1.5 and up to 3 times ULN | Withhold
Hepatitis with no tumor involvement of the liver | ALT or AST increases to more than 8 times ULN; or; total bilirubin increases to more than 3 times the ULN | Permanently discontinue
Hepatitis with tumor involvement of the liver [If AST and ALT are less than or equal to ULN at baseline in patients with liver involvement, withhold or permanently discontinue durvalumab based on recommendations for hepatitis with no liver involvement.] | AST or ALT is more than 1 and up to 3 times ULN at baseline and increases to more than 5 and up to 10 times ULN; or; AST or ALT is more than 3 and up to 5 times ULN at baseline and increases to more than 8 and up to 10 times ULN | Withhold
Hepatitis with tumor involvement of the liver [If AST and ALT are less than or equal to ULN at baseline in patients with liver involvement, withhold or permanently discontinue durvalumab based on recommendations for hepatitis with no liver involvement.] | AST or ALT increases to more than 10 times ULN; or; Total bilirubin increases to more than 3 times ULN | Permanently discontinue
Endocrinopathies | Grade 3 or 4 | Withhold until clinically stable or permanently discontinue depending on severity
Nephritis with Renal Dysfunction | Grade 2 or 3 increased blood creatinine | Withhold
Nephritis with Renal Dysfunction | Grade 4 increased blood creatinine | Permanently discontinue
Exfoliative Dermatologic Conditions | Suspected SJS, TEN, or DRESS | Withhold
Exfoliative Dermatologic Conditions | Confirmed SJS, TEN, or DRESS | Permanently discontinue
Myocarditis | Grade 2, 3, or 4 | Permanently discontinue
Neurological Toxicities | Grade 2 | Withhold
Neurological Toxicities | Grade 3 or 4 | Permanently discontinue
Other Adverse Reactions
Infusion-related reactions [see Warnings and Precautions (5.2)] | Grade 1 or 2 | Interrupt or slow the rate of infusion
Infusion-related reactions [see Warnings and Precautions (5.2)] | Grade 3 or 4 | Permanently discontinue
ALT = alanine aminotransferase, AST = aspartate aminotransferase, DRESS = Drug Rash with Eosinophilia and Systemic Symptoms, SJS = Stevens Johnson Syndrome, TEN = toxic epidermal necrolysis, ULN = upper limit normal

2.3 Preparation and Administration

Preparation

- Visually inspect drug product for particulate matter and discoloration. Discard if the solution is cloudy, discolored, or visible particles are observed.
- Do not shake the vial.
- Withdraw the required volume from the vial(s) of IMJUDO and discard the vial with any unused portion.
- Transfer into an intravenous bag containing 0.9% Sodium Chloride Injection, USP or 5% Dextrose Injection, USP and dilute to a concentration between 0.1 mg/mL and 10 mg/mL. Mix diluted solution by gentle inversion. Do not shake the solution.

Storage of Diluted IMJUDO Infusion Solution

- IMJUDO does not contain a preservative. Administer infusion solution immediately once prepared. If infusion solution is not administered immediately and needs to be stored, the total time from preparation to the start of administration should not exceed:

24 hours in a refrigerator at 2°C to 8°C (36°F to 46°F)

24 hours at room temperature up to 30°C (86°F)

- Do not freeze.
- Do not shake.

Administration

- Administer IMJUDO infusion solution intravenously over 60 minutes through an intravenous line containing a sterile, low-protein binding 0.2 or 0.22 micron filter.
- Use separate infusion bags and filters for each drug product.

IMJUDO In Combination with Other Products

- Administer all drug products as separate intravenous infusions.
- Do not co-administer other drugs through the same infusion line.
- For platinum-based chemotherapy, refer to Prescribing Information for administration information.
- For pemetrexed treatment, refer to Prescribing Information for administration information.

Combination Regimens: Order of Infusions

IMJUDO in Combination with Durvalumab

- Infuse IMJUDO, followed by durvalumab on the same day of dosing.

IMJUDO in Combination with Durvalumab and Platinum-based Chemotherapy

- Infuse IMJUDO first, followed by durvalumab and then platinum-based chemotherapy on the day of dosing.

IMJUDO in Combination with Durvalumab and Pemetrexed Therapy

- Infuse IMJUDO first, followed by durvalumab and then pemetrexed treatment on the day of dosing.

Combination Regimens: Infusion Instructions

IMJUDO in Combination with Durvalumab

- Observe patient for 60 minutes following completion of IMJUDO infusion [see Warnings and Precautions (5.2)]. Then administer durvalumab as a separate intravenous infusion over 60 minutes

IMJUDO in Combination with Durvalumab and Platinum-based Chemotherapy/ Pemetrexed Therapy

Cycle 1:

Infuse IMJUDO over one hour. One to two hours after completion of IMJUDO infusion, infuse durvalumab over one hour. One to two hours after completion of durvalumab infusion, administer platinum-based chemotherapy.

Subsequent Cycles:

If there are no infusion reactions during cycle 1, subsequent cycles of durvalumab can be given immediately after IMJUDO. The time between the end of the durvalumab infusion and the start of chemotherapy can be reduced to 30 minutes.

3 DOSAGE FORMS AND STRENGTHS

Injection: 25 mg/1.25 mL (20 mg/mL) or 300 mg/15 mL (20 mg/mL) clear to slightly opalescent, colorless to slightly yellow solution in a single-dose vial.

4 CONTRAINDICATIONS

None.

5 WARNINGS AND PRECAUTIONS

5.1 Severe and Fatal Immune-Mediated Adverse Reactions

IMJUDO is a monoclonal antibody that blocks T-cell inhibitory signals induced by the CTLA-4 pathway, thereby removing inhibition of the immune response. In combination with durvalumab, a PD-L1 inhibitor, these drugs have the potential for induction of immune-mediated adverse reactions. Immune-mediated adverse reactions listed herein may not be inclusive of all possible severe and fatal immune-mediated reactions.

Immune-mediated adverse reactions, which may be severe or fatal, can occur in any organ system or tissue. Immune-mediated adverse reactions can occur at any time after starting IMJUDO in combination with durvalumab. While immune-mediated adverse reactions usually manifest during treatment, immune-mediated adverse reactions can also manifest after discontinuation of IMJUDO and/or durvalumab.

Early identification and management of immune-mediated adverse reactions are essential to ensure safe use of IMJUDO in combination with durvalumab. Monitor for signs and symptoms that may be clinical manifestations of underlying immune-mediated adverse reactions. Evaluate clinical chemistries including liver enzymes, creatinine, adrenocorticotropic hormone (ACTH) level, and thyroid function at baseline and before each dose. Institute medical management promptly, including specialty consultation as appropriate.

Withhold or permanently discontinue IMJUDO and durvalumab depending on severity [see Dosage and Administration (2.2)]. In general, if combination of IMJUDO and durvalumab requires interruption or discontinuation, administer systemic corticosteroid therapy (1 to 2 mg/kg/day prednisone or equivalent) until improvement to Grade 1 or less. Upon improvement to Grade 1 or less, initiate corticosteroid taper and continue to taper over at least 1 month. Consider administration of other systemic immunosuppressants in patients whose immune-mediated adverse reactions are not controlled with corticosteroid therapy.

Toxicity management guidelines for adverse reactions that do not necessarily require systemic steroids (e.g., endocrinopathies and dermatologic reactions) are discussed below.

Immune-Mediated Pneumonitis

IMJUDO in combination with durvalumab can cause immune-mediated pneumonitis, which may be fatal.

IMJUDO with Durvalumab

Immune-mediated pneumonitis occurred in 1.3% (5/388) of patients receiving IMJUDO in combination with durvalumab, including fatal (0.3%) and Grade 3 (0.2%) adverse reactions. Events resolved in 3 of the 5 patients and resulted in permanent discontinuation in 1 patient. Systemic corticosteroids were required in all patients; of these, 4 patients required high-dose corticosteroid treatment (at least 40 mg prednisone or equivalent per day). One patient (1/5) required other immunosuppressants.

IMJUDO with Durvalumab and Platinum-Based Chemotherapy

Immune-mediated pneumonitis occurred in 3.5% (21/596) of patients receiving IMJUDO in combination with durvalumab and platinum-based chemotherapy, including fatal (0.5%) and Grade 3 (1%) adverse reactions. Events resolved in 11 of the 21 patients and resulted in permanent discontinuation in 7 patients. Systemic corticosteroids were required in all patients with immune-mediated pneumonitis, while 1 patient (1/21) required other immunosuppressants.

Immune-Mediated Colitis

IMJUDO in combination with durvalumab and platinum-based chemotherapy can cause immune-mediated colitis, which may be fatal.

IMJUDO in combination with durvalumab can cause immune-mediated colitis that is frequently associated with diarrhea. Cytomegalovirus (CMV) infection/reactivation has been reported in patients with corticosteroid-refractory immune-mediated colitis. In cases of corticosteroid-refractory colitis, consider repeating infectious workup to exclude alternative etiologies.

IMJUDO with Durvalumab

Immune-mediated colitis or diarrhea occurred in 6% (23/388) of patients receiving IMJUDO in combination with durvalumab, including Grade 3 (3.6%) adverse reactions. Events resolved in 22 of the 23 patients and resulted in permanent discontinuation in 5 patients. All patients received systemic corticosteroids, and 20 of the 23 patients received high-dose corticosteroid treatment (at least 40 mg prednisone or equivalent per day). Three patients also received other immunosuppressants.

Intestinal perforation has been observed in other studies of IMJUDO in combination with durvalumab.

IMJUDO with Durvalumab and Platinum-Based Chemotherapy

Immune-mediated colitis occurred in 6.5% (39/596) of patients receiving IMJUDO in combination with durvalumab and platinum-based chemotherapy, including fatal (0.2%) and Grade 3 (2.5%) adverse reactions. Events resolved in 33 of the 39 patients and resulted in permanent discontinuation in 11 patients. Systemic corticosteroids were required in all patients with immune-mediated colitis, while 4 patients (4/39) required other immunosuppressants.

Intestinal perforation and large intestine perforation were reported in 0.1% of patients receiving IMJUDO in combination with durvalumab.

Immune-Mediated Hepatitis

IMJUDO in combination with durvalumab can cause immune-mediated hepatitis, which may be fatal.

IMJUDO with Durvalumab

Immune-mediated hepatitis occurred in 7.5% (29/388) of patients receiving IMJUDO in combination with durvalumab, including fatal (0.8%), Grade 4 (0.3%), and Grade 3 (4.1%) adverse reactions. Events resolved in 12 of the 29 patients and resulted in permanent discontinuation in 9 patients. Systemic corticosteroids were required in all 29 patients and all 29 patients required high-dose corticosteroid treatment (at least 40 mg prednisone or equivalent per day). Eight patients (8/29) required other immunosuppressants.

IMJUDO with Durvalumab and Platinum-Based Chemotherapy

Immune-mediated hepatitis occurred in 3.9% (23/596) of patients receiving IMJUDO in combination with durvalumab and platinum-based chemotherapy, including fatal (0.3%), Grade 4 (0.5%), and Grade 3 (2%) adverse reactions. Events resolved in 12 of the 23 patients and resulted in permanent discontinuation in 27 patients. Systemic corticosteroids were required in all patients with immune-mediated hepatitis, while 2 patients (2/23) required use of other immunosuppressants.

Immune-Mediated Endocrinopathies

Adrenal Insufficiency: IMJUDO in combination with durvalumab can cause primary or secondary adrenal insufficiency. For Grade 2 or higher adrenal insufficiency, initiate symptomatic treatment, including hormone replacement as clinically indicated. Withhold or permanently discontinue IMJUDO in combination with durvalumab based on the severity [see Dosage and Administration (2.2)].

IMJUDO with Durvalumab

Immune-mediated adrenal insufficiency occurred in 1.5% (6/388) of patients receiving IMJUDO in combination with durvalumab, including Grade 3 (0.3%) adverse reactions. Events resolved in 2 of the 6 patients. Systemic corticosteroids were required in all 6 patients, and of these, 1 patient required high-dose corticosteroid treatment (at least 40 mg prednisone or equivalent per day).

IMJUDO with Durvalumab and Platinum-Based Chemotherapy

Immune-mediated adrenal insufficiency occurred in 2.2% (13/596) of patients receiving IMJUDO in combination with durvalumab and platinum-based chemotherapy, including Grade 3 (0.8%) adverse reactions. Events resolved in 2 of the 13 patients and resulted in permanent discontinuation in 1 patient. Systemic corticosteroids were required in all patients with adrenal insufficiency. One patient also required endocrine therapy.

Hypophysitis: IMJUDO in combination with durvalumab can cause immune-mediated hypophysitis. Hypophysitis can present with acute symptoms associated with mass effect such as headache, photophobia, or visual field cuts. Hypophysitis can cause hypopituitarism. Initiate symptomatic treatment including hormone replacement as clinically indicated. Withhold or permanently discontinue IMJUDO in combination with durvalumab depending on severity [see Dosage and Administration (2.2)].

IMJUDO with Durvalumab

Immune-mediated hypophysitis/hypopituitarism occurred in 1% (4/388) of patients receiving IMJUDO in combination with durvalumab. Events resolved in 2 of the 4 patients. Systemic corticosteroids were required in 3 patients, and of these, 1 patient received high-dose corticosteroid treatment (at least 40 mg prednisone or equivalent per day). Two patients also required endocrine therapy.

IMJUDO with Durvalumab and Platinum-Based Chemotherapy

Immune-mediated hypophysitis occurred in 1.3% (8/596) of patients receiving IMJUDO in combination with durvalumab and platinum-based chemotherapy, including Grade 3 (0.5%) adverse reactions. Events resulted in permanent discontinuation in 1 patient. Systemic corticosteroids were required in 6 patients with immune-mediated hypophysitis; of these, 2 of the 8 patients received high-dose corticosteroid treatment (at least 40 mg prednisone or equivalent per day). Four patients also required endocrine therapy.

Thyroid Disorders: IMJUDO in combination with durvalumab can cause immune-mediated thyroid disorders. Thyroiditis can present with or without endocrinopathy. Hypothyroidism can follow hyperthyroidism. Initiate hormone replacement therapy for hypothyroidism or institute medical management of hyperthyroidism as clinically indicated. Withhold or discontinue IMJUDO in combination with durvalumab based on the severity [see Dosage and Administration (2.2)].

Thyroiditis:

IMJUDO with Durvalumab

Immune-mediated thyroiditis occurred in 1.5% (6/388) of patients receiving IMJUDO in combination with durvalumab. Events resolved in 2 of the 6 patients. Systemic corticosteroids were required in 2 patients (2/6) with immune-mediated thyroiditis; of these, 1 patient required high-dose corticosteroid treatment (at least 40 mg prednisone or equivalent per day). All patients required other therapy including hormone replacement therapy, thiamazole, carbimazole, propylthiouracil, perchlorate, calcium channel blocker, or beta-blocker.

IMJUDO with Durvalumab and Platinum-Based Chemotherapy

Immune-mediated thyroiditis occurred in 1.2% (7/596) of patients receiving IMJUDO in combination with durvalumab and platinum-based chemotherapy. Events resolved in 2 of the 7 patients and one resulted in permanent discontinuation. Systemic corticosteroids were required in 2 patients (2/7) with immune-mediated thyroiditis, while all patients required endocrine therapy.

Hyperthyroidism:

IMJUDO with Durvalumab

Immune-mediated hyperthyroidism occurred in 4.6% (18/388) of patients receiving IMJUDO in combination with durvalumab, including Grade 3 (0.3%) adverse reactions. Events resolved in 15 of the 18 patients. Two patients (2/18) required high-dose corticosteroid treatment (at least 40 mg prednisone or equivalent per day). Seventeen patients required other therapy (thiamazole, carbimazole, propylthiouracil, perchlorate, calcium channel blocker, or beta-blocker).

IMJUDO with Durvalumab and Platinum-Based Chemotherapy

Immune-mediated hyperthyroidism occurred in 5% (30/596) of patients receiving IMJUDO in combination with durvalumab and platinum-based chemotherapy, including Grade 3 (0.2%) adverse reactions. Events resolved in 21 of the 30 patients. Systemic corticosteroids were required in 5 patients (5/30) with immune-mediated hyperthyroidism, while 28 patients (28/30) required endocrine therapy.

Hypothyroidism:

IMJUDO with Durvalumab

Immune-mediated hypothyroidism occurred in 11% (42/388) of patients receiving IMJUDO in combination with durvalumab. Events resolved in 5 of the 42 patients. One patient received high-dose corticosteroid treatment (at least 40 mg prednisone or equivalent per day). All patients required other therapy (thiamazole, carbimazole, propylthiouracil, perchlorate, calcium channel blocker, or beta-blocker).

IMJUDO with Durvalumab and Platinum-Based Chemotherapy

Immune-mediated hypothyroidism occurred in 8.6% (51/596) of patients receiving IMJUDO in combination with durvalumab and platinum-based chemotherapy, including Grade 3 (0.5%) adverse reactions. Systemic corticosteroids were required in 2 patients (2/51) and all patients required endocrine therapy.

Type 1 Diabetes Mellitus, Which Can Present with Diabetic Ketoacidosis: Monitor patients for hyperglycemia or other signs and symptoms of diabetes. Initiate treatment with insulin as clinically indicated. Withhold or permanently discontinue IMJUDO in combination with durvalumab based on the severity [see Dosage and Administration (2.2)].

IMJUDO with Durvalumab

Two patients (0.5%, 2/388) had events of hyperglycemia requiring insulin therapy that had not resolved at last follow-up.

IMJUDO with Durvalumab and Platinum-Based Chemotherapy

Immune-mediated Type 1 Diabetes Mellitus occurred in 0.5% (3/596) of patients receiving IMJUDO in combination with durvalumab and platinum-based chemotherapy, including Grade 3 (0.3%) adverse reactions. All patients required endocrine therapy.

Immune-Mediated Nephritis with Renal Dysfunction

IMJUDO in combination with durvalumab can cause immune-mediated nephritis.

IMJUDO with Durvalumab

Immune-mediated nephritis occurred in 1% (4/388) of patients receiving IMJUDO in combination with durvalumab, including Grade 3 (0.5%) adverse reactions. Events resolved in 3 of the 4 patients and resulted in permanent discontinuation in 2 patients. Systemic corticosteroids were required in all patients with immune-mediated nephritis; of these, 3 patients required high-dose corticosteroid treatment (at least 40 mg prednisone or equivalent per day).

IMJUDO with Durvalumab and Platinum-Based Chemotherapy

Immune-mediated nephritis occurred in 0.7% (4/596) of patients receiving IMJUDO in combination with durvalumab and platinum-based chemotherapy, including Grade 3 (0.2%) adverse reactions. Events resolved in 1 of the 4 patients and resulted in permanent discontinuation in 3 patients. Systemic corticosteroids were required in all patients with immune-mediated nephritis.

Immune-Mediated Dermatology Reactions

IMJUDO in combination with durvalumab can cause immune-mediated rash or dermatitis. Exfoliative dermatitis, including Stevens Johnson Syndrome (SJS), drug rash with eosinophilia and systemic symptoms (DRESS), and toxic epidermal necrolysis (TEN), has occurred with CTLA-4 and PD-1/L-1 blocking antibodies. Topical emollients and/or topical corticosteroids may be adequate to treat mild to moderate non-exfoliative rashes. Withhold or permanently discontinue IMJUDO in combination with durvalumab depending on severity [see Dosage and Administration (2.2)].

IMJUDO with Durvalumab

Immune-mediated rash or dermatitis occurred in 4.9% (19/388) of patients receiving IMJUDO in combination with durvalumab, including Grade 4 (0.3%) and Grade 3 (1.5%) adverse reactions. Events resolved in 13 of the 19 patients and resulted in permanent discontinuation in 2 patients. Systemic corticosteroids were required in all patients with immune-mediated rash or dermatitis; of these, 12 patients required high-dose corticosteroid treatment (at least 40 mg prednisone or equivalent per day). One patient received other immunosuppressants.

IMJUDO with Durvalumab and Platinum-Based Chemotherapy

Immune-mediated rash or dermatitis occurred in 7.2% (43/596) of patients receiving IMJUDO in combination with durvalumab and platinum-based chemotherapy, including Grade 3 (0.3%) adverse reactions. Events resolved in 32 of the 43 patients and resulted in permanent discontinuation in 2 patients. Systemic corticosteroids were required in all patients with immune-mediated rash or dermatitis.

Immune-Mediated Pancreatitis

IMJUDO in combination with durvalumab can cause immune-mediated pancreatitis.

IMJUDO with Durvalumab

Immune-mediated pancreatitis occurred in 2.3% (9/388) of patients receiving IMJUDO in combination with durvalumab, including Grade 4 (0.3%) and Grade 3 (1.5%) adverse reactions. Events resolved in 6 of the 9 patients. Systemic corticosteroids were required in all 9 patients and of these, 7 patients required high-dose corticosteroid treatment (at least 40 mg prednisone or equivalent per day).

Other Immune-Mediated Adverse Reactions

The following clinically significant, immune-mediated adverse reactions occurred at an incidence of less than 1% each in patients who received IMJUDO in combination with durvalumab or were reported with the use of other immune-checkpoint inhibitors.

Cardiac/vascular: Myocarditis, pericarditis, vasculitis.

Nervous system: Meningitis, encephalitis, myelitis and demyelination, myasthenic syndrome/myasthenia gravis (including exacerbation), Guillain-Barré syndrome, nerve paresis, autoimmune neuropathy.

Ocular: Uveitis, iritis, and other ocular inflammatory toxicities can occur. Some cases can be associated with retinal detachment. Various grades of visual impairment to include blindness can occur. If uveitis occurs in combination with other immune-mediated adverse reactions, consider a Vogt-Koyanagi-Harada-like syndrome, as this may require treatment with systemic steroids to reduce the risk of permanent vision loss.

Gastrointestinal: Gastritis, duodenitis.

Musculoskeletal and connective tissue disorders: Myositis/polymyositis, rhabdomyolysis and associated sequelae including renal failure, arthritis, polymyalgia rheumatica.

Endocrine: Hypoparathyroidism.

Other (hematologic/immune): Hemolytic anemia, aplastic anemia, hemophagocytic lymphohistiocytosis, systemic inflammatory response syndrome, histiocytic necrotizing lymphadenitis (Kikuchi lymphadenitis), sarcoidosis, and immune thrombocytopenia.

5.2 Infusion-Related Reactions

IMJUDO in combination with durvalumab can cause severe or life-threatening infusion-related reactions.

Monitor for signs and symptoms of infusion-related reactions. Interrupt, slow the rate of, or permanently discontinue IMJUDO and durvalumab based on the severity [see Dosage and Administration (2.2)]. For Grade 1 or 2 infusion-related reactions, consider using pre-medications with subsequent doses.

IMJUDO with Durvalumab

Infusion-related reactions occurred in 10 (2.6%) patients receiving IMJUDO in combination with durvalumab.

IMJUDO with Durvalumab and Platinum-Based Chemotherapy

Infusion-related reactions occurred in 2.9% (17/596) of patients receiving IMJUDO in combination with durvalumab and platinum-based chemotherapy, including Grade 3 (0.3%) adverse reactions.

5.3 Embryo-Fetal Toxicity

Based on findings from animal studies and its mechanism of action, IMJUDO can cause fetal harm when administered to a pregnant woman. In animal studies, CTLA-4 blockade is associated with higher incidence of pregnancy loss.

Advise pregnant women and females of reproductive potential of the potential risk to a fetus. Advise females of reproductive potential to use effective contraception during treatment with IMJUDO and for 3 months after the last dose of IMJUDO [see Use in Specific Populations (8.1, 8.3)].

6 ADVERSE REACTIONS

The following adverse reactions are discussed in greater detail in other sections of the labeling.

- Immune-Mediated Adverse Reactions [see Warnings and Precautions (5.1)].
- Infusion-Related Reactions [see Warnings and Precautions (5.2)].

6.1 Clinical Trials Experience

Because clinical trials are conducted under widely varying conditions, adverse reaction rates observed in clinical trials of a drug cannot be directly compared to rates in the clinical trials of another drug and may not reflect the rates observed in practice.

The data described in the Warnings and Precautions reflect exposure to IMJUDO 300 mg in combination with durvalumab 1,500 mg in 388 patients in HIMALAYA. In the HIMALAYA study patients received IMJUDO 300 mg administered as a single intravenous infusion in combination with durvalumab 1,500 mg on the same day, followed by durvalumab every 4 weeks.

The data also reflects exposure to IMJUDO 75 mg in combination with durvalumab 1,500 mg and histology-based platinum chemotherapy regimens in the pooled safety population (N=596) of 330 patients in POSEIDON [see Clinical Studies (14.1)], and 266 patients in CASPIAN who received up to four cycles of platinum-etoposide plus durvalumab 1,500 mg with tremelimumab-actl 75 mg every 3 weeks, followed by durvalumab 1,500 mg every 4 weeks (an unapproved regimen for extensive-stage small cell lung cancer). Of these patients, 64% received the maximum of 5 doses of IMJUDO and 79% received at least 4 doses.

In this pooled safety population, the most common (> 20%) adverse reactions were nausea (37%), decreased appetite (25%), and fatigue (22%). In this pooled safety population, the most common Grade 3 or 4 (> 10%) laboratory abnormalities were neutropenia (39%), leukopenia (21%), lymphocytopenia (20%), anemia (20%), hyponatremia (14%), lipase increased (12%), and thrombocytopenia (11%).

The data described in this section reflect exposure to IMJUDO in patients with uHCC included in the HIMALAYA study and in patients with metastatic NSCLC enrolled in the POSEIDON study.

Hepatocellular Carcinoma

Unresectable HCC - HIMALAYA

The safety of IMJUDO administered in combination with durvalumab was evaluated in a total of 388 patients with uHCC in HIMALAYA, a randomized, open-label, multicenter study [see Clinical Studies (14.1)]. Patients received IMJUDO 300 mg administered as a single intravenous infusion in combination with durvalumab 1,500 mg on the same day, followed by durvalumab every 4 weeks or sorafenib 400 mg given orally twice daily.

Serious adverse reactions occurred in 41% of patients who received IMJUDO in combination with durvalumab. Serious adverse reactions in > 1% of patients included hemorrhage (6%), diarrhea (4%), sepsis (2.1%), pneumonia (2.1%), rash (1.5%), vomiting (1.3%), acute kidney injury (1.3%), and anemia (1.3%). Fatal adverse reactions occurred in 8% of patients who received IMJUDO in combination with durvalumab, including death (1%), hemorrhage intracranial (0.5%), cardiac arrest (0.5%), pneumonitis (0.5%), hepatic failure (0.5%), and immune-mediated hepatitis (0.5%). The most common adverse reactions (occurring in ≥ 20% of patients) were rash, diarrhea, fatigue, pruritus, musculoskeletal pain, and abdominal pain.

Permanent discontinuation of the treatment regimen due to an adverse reaction occurred in 14% of patients; the most common adverse reactions leading to treatment discontinuation (≥ 1%) were hemorrhage (1.8%), diarrhea (1.5%), AST increased (1%), and hepatitis (1%).

Dosage interruptions or delay of the treatment regimen due to an adverse reaction occurred in 35% of patients. Adverse reactions which required dosage interruption or delay in ≥ 1% of patients included ALT increased (3.6%), diarrhea (3.6%), rash (3.6%), amylase increased (3.4%), AST increased (3.1%), lipase increased (2.8%), pneumonia (1.5%), hepatitis (1.5%), pyrexia (1.5%), anemia (1.3%), thrombocytopenia (1%), hyperthyroidism (1%), pneumonitis (1%), and blood creatinine increased (1%).

Table 5 summarizes the adverse reactions that occurred in patients treated with IMJUDO in combination with durvalumab in the HIMALAYA study.

Table 5. Adverse Reactions Occurring in ≥ 10% Patients in the HIMALAYA study
 | IMJUDO and Durvalumab (N=388) |  | Sorafenib (N=374)
Adverse Reaction | All Grades (%) | Grade 3-4 (%) | All Grades (%) | Grade 3-4 (%)
Gastrointestinal disorders
Diarrhea [Represents a composite of multiple related terms.] | 27 | 6 | 45 | 4.3
Abdominal pain | 20 | 1.8 | 24 | 4
Nausea | 12 | 0 | 14 | 0
Skin and subcutaneous tissue disorders
Rash | 32 | 2.8 | 57 | 12
Pruritus | 23 | 0 | 6 | 0.3
Metabolism and nutrition disorders
Decreased appetite | 17 | 1.3 | 18 | 0.8
General disorders and administration site conditions
Fatigue | 26 | 3.9 | 30 | 6
Pyrexia | 13 | 0.3 | 9 | 0.3
Psychiatric disorders
Insomnia | 10 | 0.3 | 4.3 | 0
Endocrine disorders
Hypothyroidism | 14 | 0 | 6 | 0
Musculoskeletal and Connective Tissue Disorders
Musculoskeletal pain | 22 | 2.6 | 17 | 0.8

Table 6 summarizes the laboratory abnormalities that occurred in patients treated with IMJUDO in combination with durvalumab in the HIMALAYA study.

Table 6. Laboratory Abnormalities Worsening from Baseline Occurring in ≥ 20% of Patients in the HIMALAYA study
 | IMJUDO and Durvalumab |  | Sorafenib
Laboratory Abnormality | Any grade; (%) | Grade 3 or 4; (%) | Any grade; (%) | Grade 3 or 4; (%)
Chemistry
Aspartate Aminotransferase increased | 63 | 27 | 55 | 21
Alanine Aminotransferase increased | 56 | 18 | 53 | 12
Sodium decreased | 46 | 15 | 40 | 11
Bilirubin increased | 41 | 8 | 47 | 11
Alkaline Phosphatase increased | 41 | 8 | 44 | 5
Glucose increased | 39 | 14 | 29 | 4
Calcium decreased | 34 | 0 | 43 | 0.3
Albumin decreased | 31 | 0.5 | 37 | 1.7
Potassium increased | 28 | 3.8 | 21 | 2.6
Creatinine increased | 21 | 1.3 | 15 | 0.9
Hematology
Hemoglobin decreased | 52 | 4.8 | 40 | 6
Lymphocytes decreased | 41 | 11 | 39 | 10
Platelets decreased | 29 | 1.6 | 35 | 3.1
Leukocytes decreased | 20 | 0.8 | 30 | 1.1

Non-Small Cell Lung Cancer

Metastatic NSCLC – POSEIDON

The safety of IMJUDO in combination with durvalumab and platinum-based chemotherapy in patients with metastatic NSCLC was evaluated in POSEIDON (NCT03164616), a randomized, open-label, multicenter, active-controlled trial. A total of 330 patients received IMJUDO (≥ 30 kg body weight received 75 mg and ≤ 30kg body weight received 1 mg/kg) in combination with durvalumab 1,500 mg and histology-based platinum chemotherapy regimens [see Clinical Studies (14.2)]. Of these patients, 66% received up to the maximum 5 doses of IMJUDO and 79% received at least 4 doses. Treatment was continued with durvalumab as a single agent (or with durvalumab and histology-based pemetrexed for non-squamous patients, based on the investigator’s decision) until disease progression or unacceptable toxicity. The trial excluded patients with active or prior autoimmune disease or with medical conditions that required systemic corticosteroids or immunosuppressants [see Clinical Studies (14.2)].

The median age of patients who received IMJUDO in combination with durvalumab and platinum-based chemotherapy was 63 years (range: 27 to 87); 80% male; 61% White, 29% Asian, 58% former smoker, 25% current smoker, and 68% ECOG performance of 1.

Serious adverse reactions occurred in 44% of patients receiving IMJUDO in combination with durvalumab and platinum-based chemotherapy. The most frequent serious adverse reactions reported in at least 2% of patients were pneumonia (11%), anemia (5%), diarrhea (2.4%), thrombocytopenia (2.4%), pyrexia (2.4%), and febrile neutropenia (2.1%). Fatal adverse reactions occurred in a total of 4.2% of patients receiving IMJUDO in combination with durvalumab and platinum-based chemotherapy. These include hepatitis, nephritis, myocarditis, pancreatitis (all in the same patient), death (2 patients), sepsis (2 patients), pneumonitis (2 patients), acute kidney injury (2 patients), febrile neutropenia (1 patient), chronic obstructive pulmonary disease (1 patient), dyspnea (1 patient), sudden death (1 patient), and ischemic stroke (1 patient).

Permanent discontinuation of IMJUDO or durvalumab due to an adverse reaction occurred in 17% of the patients. Adverse reactions which resulted in permanent discontinuation of IMJUDO or durvalumab in > 2% of patients included pneumonia.

Dosage interruptions or delay of IMJUDO and durvalumab due to an adverse reaction occurred in 41% of patients. Adverse reactions which required dosage interruption or delay of IMJUDO and durvalumab in > 1% of patients included anemia, leukopenia/white blood cell count decreased, pneumonia, pneumonitis, colitis, diarrhea, hepatitis, rash, asthenia, amylase increased, alanine aminotransferase increased, aspartate aminotransferase increased, lipase increased, neutropenia/neutrophil count decreased, and thrombocytopenia/platelet count decreased.

The most common adverse reactions (occurring in ≥ 20% of patients) were nausea, fatigue, musculoskeletal pain, decreased appetite, rash, and diarrhea. Grade 3 or 4 laboratory abnormalities (≥ 10%) were neutropenia, anemia, leukopenia, lymphocytopenia, lipase increased, hyponatremia and thrombocytopenia.

Table 7 summarizes the adverse reactions in POSEIDON.

Table 7. Adverse Reactions (≥ 10%) in Patients with NSCLC Who Received IMJUDO in the POSEIDON Study
 | IMJUDO with durvalumab and platinum-based chemotherapy; N = 330 |  | Platinum-based chemotherapy; N = 333
Adverse Reaction | All Grades (%) | Grade 3 or 4 (%) | All Grades (%) | Grade 3 or 4 (%)
Respiratory, thoracic and mediastinal disorders
Cough/Productive Cough [Includes cough and productive cough.] | 12 | 0 | 8 | 0.3
Gastrointestinal disorders
Nausea | 42 | 1.8 | 37 | 2.1
Diarrhea | 22 | 1.5 | 15 | 1.5
Constipation | 19 | 0 | 24 | 0.6
Vomiting | 18 | 1.2 | 14 | 1.5
Stomatitis [Includes mucosal inflammation and stomatitis.] | 10 | 0 | 6 | 0.3
Endocrine disorders
Hypothyroidism [Includes blood thyroid stimulating hormone increased and hypothyroidism.] | 13 | 0 | 2.1 | 0
Skin and subcutaneous tissue disorders
Rash [Includes eczema, erythema, dermatitis, drug eruption, erythema multiforme, pemphigoid, rash, rash maculo-papular, rash papular, rash pruritic and rash pustular.] | 27 | 2.4 | 10 | 0.6
Alopecia | 10 | 0 | 6 | 0
Pruritus | 11 | 0 | 4.5 | 0
General disorders and administration site conditions
Fatigue/Asthenia [Includes asthenia and fatigue.] | 36 | 5 | 32 | 4.5
Pyrexia [Includes body temperature increased, hyperpyrexia, hyperthermia, and pyrexia.] | 19 | 0 | 8 | 0
Edema [Includes face edema, localized edema, and edema peripheral.] | 10 | 0 | 10 | 0.6
Musculoskeletal and connective tissue disorders
Musculoskeletal Pain [Includes arthralgia, arthritis, back pain, bone pain, musculoskeletal chest pain, musculoskeletal pain, myalgia, neck pain, non-cardiac chest pain, spinal pain.] | 29 | 0.6 | 22 | 1.5
Metabolism and nutrition disorders
Decreased appetite | 28 | 1.5 | 25 | 1.2
Infections and Infestations
Pneumonia [Includes lower respiratory tract infection, pneumocystis jirovecii pneumonia, pneumonia, pneumonia aspiration, pneumonia bacterial.] | 17 | 8 | 12 | 4.2
Upper respiratory tract infections [Includes laryngitis, nasopharyngitis, pharyngitis, rhinitis, sinusitis, tonsillitis, tracheobronchitis and upper respiratory tract infection.] | 15 | 0.6 | 9 | 0.9
Nervous system disorders
Headache [Includes headache, migraine.] | 11 | 0 | 8 | 0.6

Table 8 summarizes the laboratory abnormalities in POSEIDON.

Table 8: Select Laboratory Abnormalities (≥ 10%) That Worsened from Baseline in Patients with NSCLC Who Received IMJUDO in the POSEIDON Study
Laboratory Abnormality | IMJUDO with Durvalumab and Platinum-based chemotherapy |  | Platinum-based chemotherapy
Laboratory Abnormality | All Grades (%) | Grade 3 or 4 (%) | All Grades; (%) | Grade 3 or 4; (%)
Chemistry
Lipase increased | 35 | 14 | 25 | 5
Hyponatremia | 55 | 13 | 50 | 11
Hypernatremia | 15 | 0 | 14 | 0
Amylase increased | 41 | 9 | 25 | 6
Hypokalemia | 21 | 7 | 17 | 2.8
Hyperglycemia | 42 | 6 | 37 | 3.1
Increased ALT | 64 | 6 | 56 | 4.7
Increased AST | 63 | 5 | 55 | 2.2
Blood creatinine increased | 89 | 4.0 | 83 | 1.9
Increased Alkaline Phosphatase | 33 | 3.4 | 26 | 1.2
Gamma Glutamyl Transferase increased | 38 | 2.2 | 35 | 4.7
Hyperkalemia | 49 | 2.2 | 35 | 2.8
Albumin decreased | 27 | 1.9 | 18 | 0.9
Hypocalcemia | 58 | 0.9 | 49 | 0.9
Hypomagnesemia | 12 | 4 | 23 | 0
Bilirubinemia | 16 | 0.9 | 8 | 0.3
Hematology
Neutropenia | 71 | 37 | 69 | 32
Anemia | 84 | 24 | 84 | 25
Leukopenia | 77 | 21 | 81 | 18
Lymphocytopenia | 67 | 20 | 60 | 19
Thrombocytopenia | 53 | 11 | 54 | 12

8 USE IN SPECIFIC POPULATIONS

8.1 Pregnancy

Risk summary

Based on findings from animal studies and its mechanism of action, IMJUDO can cause fetal harm when administered to a pregnant woman [see Clinical Pharmacology (12.1)]. There are no available data on the use of IMJUDO in pregnant women. In animal studies, CTLA-4 blockade is associated with increased risk of immune-mediated rejection of the developing fetus and fetal death (see Data).

Human immunoglobulin G2 (IgG2) is known to cross the placental barrier; therefore, IMJUDO has the potential to be transmitted from the mother to the developing fetus. Advise pregnant women and females of reproductive potential of the potential risk to a fetus.

In the U.S. general population, the estimated background risk of major birth defects and miscarriage in clinically recognized pregnancies is 2% to 4% and 15% to 20%, respectively.

Data

Animal Data

In a reproduction study, administration of tremelimumab-actl to pregnant cynomolgus monkeys during the period of organogenesis was not associated with maternal toxicity or effects on embryo-fetal development at exposure levels approximately 4 to 31-times higher than those observed at a recommended dose range of 75 mg to 300 mg based on area under the curve (AUC). CTLA-4 plays a role in maintaining maternal immune tolerance to the fetus to preserve pregnancy and in immune regulation of the newborn. In a murine model of pregnancy, CTLA-4 blockade resulted in increased resorptions and reduced live fetuses. Mated genetically engineered mice heterozygous for CTLA-4 (CTLA-4+/-) gave birth to CTLA-4+/- offspring and offspring deficient in CTLA-4 (homozygous negative, CTLA-4-/-) that appeared healthy at birth. The CTLA-4-/- homozygous negative offspring developed signs of a lymphoproliferative disorder and died by 3 to 4 weeks of age with multiorgan tissue destruction. Based on its mechanism of action, fetal exposure to tremelimumab-actl may increase the risk of developing immune-mediated disorders or altering the normal immune response.

8.2 Lactation

Risk Summary

There are no data on the presence of tremelimumab-actl in human milk, its effects on a breastfed child, or on milk production. Maternal IgG is known to be present in human milk. The effects of local gastrointestinal exposure and limited systemic exposure in the breastfed child to IMJUDO are unknown. Because of the potential for serious adverse reactions in the breastfed child, advise women not to breastfeed during treatment with IMJUDO and for 3 months after the last dose. Refer to the Prescribing Information for agents administered in combination with IMJUDO for breastfeeding recommendations, as appropriate.

8.3 Females and Males of Reproductive Potential

IMJUDO can cause fetal harm when administered to a pregnant woman [see Use in Specific Populations (8.1)].

Pregnancy Testing

Verify pregnancy status of females of reproductive potential prior to initiating treatment with IMJUDO.

Contraception

Advise females of reproductive potential to use effective contraception during treatment with IMJUDO and for 3 months after the last dose. Refer to the Prescribing Information for the agents administered in combination with IMJUDO for recommended contraception duration, as appropriate.

8.4 Pediatric Use

The safety and effectiveness of IMJUDO have not been established in pediatric patients. Safety and efficacy were assessed but not established in a multi-center, open-label study (NCT03837899) in which 41 pediatric patients aged 1 to < 17 years with advanced solid tumors received IMJUDO in combination with durvalumab. No new safety signals were observed in pediatric patients in this study.

Tremelimumab-actl systemic exposure in pediatric patients ≥ 35 kg was within the range of the values previously observed in adults given the same weight-based dose, whereas the systemic exposure in pediatric patients < 35 kg was lower than that of adults.

8.5 Geriatric Use

Of the 393 patients with uHCC treated with IMJUDO in combination with durvalumab, 50% of patients were 65 years or older and 13% of patients were 75 years or older. No overall differences in safety or efficacy of IMJUDO have been observed between patients 65 years or older and younger adult patients.

Of the 330 patients with metastatic NSCLC treated with IMJUDO in combination with durvalumab and platinum-based chemotherapy, 143 (43%) patients were 65 years or older and 35 (11%) patients were 75 years or older. No overall differences in safety or effectiveness were observed between these subjects and younger subjects.

11 DESCRIPTION

Tremelimumab-actl, a cytotoxic T-lymphocyte-associated antigen 4 (CTLA-4) blocking human IgG2 monoclonal antibody, is produced by recombinant DNA technology in NS0 cell suspension culture and has a molecular weight of 149 kDa.

IMJUDO (tremelimumab-actl) injection is a sterile, preservative-free, clear to slightly opalescent, colorless to slightly yellow solution, in a single-dose vial for intravenous infusion after dilution. IMJUDO contains tremelimumab-actl at a concentration of 20 mg/mL in either a 25 mg/1.25 mL or a 300 mg/15 mL single-dose vial.

Each mL contains 20 mg of tremelimumab-actl, and edetate disodium (0.09 mg), histidine (0.68 mg), L‑histidine hydrochloride monohydrate (3.3 mg), polysorbate 80 (0.2 mg), trehalose (76 mg), and Water for Injection, USP. The pH is approximately 5.5.

12 CLINICAL PHARMACOLOGY

12.1 Mechanism of Action

CTLA-4 is a negative regulator of T-cell activity. Tremelimumab-actl is a monoclonal antibody that binds to CTLA-4 and blocks the interaction with its ligands CD80 and CD86, releasing CTLA-4-mediated inhibition of T-cell activation. In synergistic mouse tumor models, blocking CTLA-4 activity resulted in decreased tumor growth and increased proliferation of T cells in tumors.

12.2 Pharmacodynamics

The exposure-response relationship and time course of pharmacodynamic response for the safety and effectiveness of tremelimumab-actl have not been fully characterized.

12.3 Pharmacokinetics

The pharmacokinetics of tremelimumab-actl was studied in patients with other solid tumors following administration of doses 1 mg/kg, 3 mg/kg, and 10 mg/kg (1- to 10-times the approved recommended dosage) administered once every 4 weeks for 4 doses. The pharmacokinetics of tremelimumab-actl as a single dose of 300 mg were evaluated in patients with HCC.

The AUC of tremelimumab-actl increased proportionally from 1 mg/kg to 10 mg/kg every 4 weeks (1 to 10-times the approved recommended dosage) and steady state was achieved at approximately 12 weeks.

Distribution

The geometric mean (% coefficient of variation [CV%]) of tremelimumab-actl for central (V1) and peripheral (V2) volume of distribution was 3.45 (24%) and 2.66 (34%) L, respectively.

Elimination

The geometric mean (CV%) terminal half-life of tremelimumab-actl was 16.9 days (19%) after a single dose and 18.2 days (19%) during steady state. The geometric mean (CV%) clearance of tremelimumab-actl was 0.286 L/day (32%) after a single dose and 0.263 L/day (32%) during steady state.

Specific Populations

There were no clinically significant differences in the pharmacokinetics of tremelimumab-actl based on body weight (34 to149 kg), age (18 to 87 years), sex, race (White, Black, Asian, Native Hawaiian, Pacific Islander, or American Indian), serum albumin levels (0.3 to 396 g/L), lactate dehydrogenase levels (12 to 5570 U/L), soluble PD-L1 (67 to 349 pg/mL), tumor type (NSCLC, HCC), organ dysfunction including mild to moderate renal impairment (CLcr 30 to 89 mL/min), and mild to moderate hepatic impairment (bilirubin < 3 x ULN and any AST).

The effect of severe renal impairment (CLcr 15 to 29 mL/min) or severe hepatic impairment (bilirubin > 3 x ULN and any AST) on the pharmacokinetics of tremelimumab-actl is unknown.

12.6 Immunogenicity

The observed incidence of anti-drug antibodies (ADA) is highly dependent on the sensitivity and specificity of the assay. Differences in assay methods preclude meaningful comparisons of the incidence of ADA in the studies described below with the incidence of ADA in other studies, including those of tremelimumab-actl.

In the HIMALAYA study, of the 182 patients who were treated with a single dose of tremelimumab-actl in combination with durvalumab once in every 4 weeks therapy and evaluable for the presence of ADAs against tremelimumab-actl at predose week 0 and week 4, 11% (20/182) of patients tested positive for anti-tremelimumab-actl antibodies. Among the 20 patients who tested positive for ADAs 40% (8/20) tested positive for neutralizing antibodies against tremelimumab-actl. There was no identified clinically significant effect of anti-tremelimumab-actl antibodies on the pharmacokinetics or safety of tremelimumab-actl; however, the effect of ADAs and neutralizing antibodies on the effectiveness of tremelimumab-actl is unknown.

In the POSEIDON study, of the 278 ADA-evaluable patients who were treated with IMJUDO 75 mg for up to five doses in combination with durvalumab 1,500 mg and platinum-based chemotherapy every 3 weeks and evaluated for presence of ADAs against tremelimumab-actl at pre-dose week 0, week 3, and week 12, 14% (38/278) of patients tested positive for anti-tremelimumab-actl antibodies. Among the 38 patients who tested positive for ADAs, 82% (31/38) tested positive for neutralizing antibodies against tremelimumab-actl. There was no identified clinically significant effect of anti-tremelimumab-actl antibodies on pharmacokinetics or safety of tremelimumab-actl, however, the effect of ADAs on effectiveness of tremelimumab-actl is unknown.

13 NONCLINICAL TOXICOLOGY

13.1 Carcinogenesis, Mutagenesis, Impairment of Fertility

The carcinogenic and genotoxic potential of tremelimumab-actl have not been evaluated.

Animal fertility studies have not been conducted with tremelimumab-actl.

14 CLINICAL STUDIES

14.1 Hepatocellular Carcinoma (HCC)

Unresectable HCC - HIMALAYA

The efficacy of IMJUDO in combination with durvalumab was evaluated in the HIMALAYA study (NCT03298451), a randomized (1:1:1), open-label, multicenter study in patients with confirmed uHCC who had not received prior systemic treatment for HCC. Patients were randomized to one of two investigational arms (IMJUDO plus durvalumab or durvalumab) or sorafenib. Study treatment consisted of IMJUDO as a one-time single intravenous infusion of 300 mg in combination with durvalumab 1,500 mg on the same day, followed by durvalumab every 4 weeks; durvalumab 1,500 mg every 4 weeks; or sorafenib 400 mg given orally twice daily, until disease progression or unacceptable toxicity. The efficacy assessment of IMJUDO is based on patients randomized to the IMJUDO plus durvalumab arm versus the sorafenib arm. Randomization was stratified by macrovascular invasion (MVI) (yes or no), etiology of liver disease (hepatitis B virus vs. hepatitis C virus vs. others) and ECOG performance status (0 vs. 1).

The study enrolled patients with BCLC Stage C or B (not eligible for locoregional therapy). The study excluded patients with co-infection of viral hepatitis B and hepatitis C; active or prior documented gastrointestinal (GI) bleeding within 12 months; ascites requiring non-pharmacologic intervention within 6 months; hepatic encephalopathy within 12 months before the start of treatment; active or prior documented autoimmune or inflammatory disorders. Esophagogastroduodenoscopy was not mandated prior to enrollment but adequate endoscopic therapy, according to institutional standards, was required for patients with a history of esophageal variceal bleeding or those assessed as high risk for esophageal variceal bleeding by the treating physician.

Study treatment was permitted beyond disease progression if the patient was clinically stable and was deriving clinical benefit as determined by the investigator.

The major efficacy outcome measure was overall survival (OS) between the IMJUDO plus durvalumab arm versus the sorafenib arm. Additional efficacy outcomes were investigator-assessed progression-free survival (PFS), objective response rate (ORR) and duration of response (DoR) according to RECIST v1.1. Tumor assessments were conducted every 8 weeks for the first 12 months and then every 12 weeks thereafter.

The baseline demographics of the IMJUDO plus durvalumab and sorafenib arms were as follows: male (85%), age < 65 years (50%), median age of 65 years (range: 18 to 88 years), White (46%), Asian (49%), Black or African American (2%), Native Hawaiian or other Pacific Islander (0.1%), race Unknown (2%), Hispanic or Latino (5%), Not Hispanic or Latino (94%), ethnicity Unknown (1%), ECOG PS 0 (62%); Child-Pugh Class score A (99%), macrovascular invasion (26%), extrahepatic spread (53%), viral etiology hepatitis B (31%), hepatitis C (27%), uninfected (42%).

Efficacy results are presented in Table 9 and Figure 1.

Table 9. Efficacy Results for HIMALAYA Study
Endpoint | IMJUDO and Durvalumab; (N=393) | Sorafenib; (N=389)
OS
Number of deaths (%) | 262 (66.7) | 293 (75.3)
Median OS (months) (95% CI) | 16.4; (14.2, 19.6) | 13.8; (12.3, 16.1)
HR (95% CI) [HR (IMJUDO and durvalumab vs. sorafenib) based on the stratified Cox proportional hazard model.] | 0.78 (0.66, 0.92)
p-value [Based on a stratified log-rank test.] [Based on a Lan-DeMets alpha spending function with O'Brien Fleming type boundary and the actual number of events observed, the boundary for declaring statistical significance for IMJUDO and durvalumab vs. sorafenib was 0.0398 (Lan and DeMets 1983).] | 0.0035
PFS
Number of events (%) | 335 (85.2) | 327 (84.1)
Median PFS (months); (95% CI) | 3.8; (3.7, 5.3) | 4.1; (3.7, 5.5)
HR (95% CI) | 0.90 (0.77, 1.05)
ORR
ORR % (95% CI) [Confirmed complete response or partial response.] [Based on Clopper-Pearson method.] | 20.1 (16.3, 24.4) | 5.1 (3.2, 7.8)
Complete Response n (%) | 12 (3.1) | 0
Partial Response n (%) | 67 (17.0) | 20 (5.1)
DoR
Median DoR (months) (95% CI) | 22.3 (13.7, NR) | 18.4 (6.5, 26.0)
% with duration ≥ 6 months | 82.3 | 78.9
% with duration ≥ 12 months | 65.8 | 63.2

CI=Confidence Interval, HR=Hazard Ratio, NR=Not Reached

Figure 1. Kaplan-Meier curve of OS

14.2 Metastatic NSCLC

Metastatic NSCLC – POSEIDON

The efficacy of IMJUDO in combination with durvalumab and platinum-based chemotherapy in previously untreated metastatic NSCLC patients with no sensitizing epidermal growth factor receptor (EGFR) mutation or anaplastic lymphoma kinase (ALK) genomic tumor aberrations was investigated in POSEIDON, a randomized, multicenter, active-controlled, open-label trial (NCT03164616). Eligible patients had Eastern Cooperative Oncology Group (ECOG) Performance Status of 0 or 1 and must have had no prior chemotherapy or any other systemic therapy for metastatic NSCLC. Choice of platinum-based chemotherapy was at the Investigator’s discretion, taking into consideration the calculated creatinine clearance. Patients with active and/or untreated brain metastases; a history of active primary immunodeficiency; autoimmune disorders including active or prior documented autoimmune or inflammatory disorders; use of systemic immunosuppressants within 14 days before the first dose of the treatment except physiological dose of systemic corticosteroids were ineligible.

Randomization was stratified by tumor cells (TC) PD-L1 expression (TC ≥ 50% vs. TC < 50%), disease stage (Stage IVA vs. Stage IVB), and histology (non-squamous vs. squamous).

Patients were randomized 1:1:1 to receive IMJUDO in combination with durvalumab and platinum-based chemotherapy according to the regimens listed below, durvalumab and platinum-based chemotherapy (an unapproved regimen for metastatic NSCLC), or platinum-based chemotherapy. The evaluation of efficacy for metastatic NSCLC relied on comparison between:

- IMJUDO 75 mg (or 1mg/kg for patients < 30kg) with durvalumab 1,500 mg and platinum-based chemotherapy every 3 weeks for 4 cycles, followed by durvalumab 1,500 mg every 4 weeks as a single agent. A fifth dose of IMJUDO 75 mg (or 1mg/kg for patients < 30kg) was given at Week 16 in combination with durvalumab dose 6.
- Platinum-based chemotherapy every 3 weeks as monotherapy for 4 cycles. Patients could receive an additional 2 cycles (a total of 6 cycles post-randomization), as clinically indicated, at Investigator’s discretion.

Patients received IMJUDO and durvalumab in combination with one of the following platinum-based chemotherapy regimens:

- Non-squamous NSCLC

Pemetrexed 500 mg/m^2 with carboplatin AUC 5-6 or cisplatin 75 mg/m^2 every 3 weeks for 4 cycles

- Squamous NSCLC

Gemcitabine 1,000 or 1,250 mg/m^2 on Days 1 and 8 with cisplatin 75 mg/m^2 or carboplatin AUC 5-6 on Day 1 every 3 weeks for 4 cycles

- Non-squamous and Squamous NSCLC

Nab-paclitaxel 100 mg/m^2 on Days 1, 8, and 15 with carboplatin AUC 5-6 on Day 1 every 3 weeks for 4 cycles

IMJUDO was given up to a maximum of 5 doses. Durvalumab and histology-based pemetrexed continued every 4 weeks until disease progression or unacceptable toxicity. Administration of durvalumab monotherapy was permitted beyond disease progression if the patient was clinically stable and deriving clinical benefit as determined by the Investigator. Patients with disease progression during durvalumab monotherapy were given the option to be retreated with 4 additional cycles of IMJUDO in combination with durvalumab. Tumor assessments were performed at Week 6, Week 12, and then every 8 weeks thereafter.

The major efficacy outcome measures were progression free survival (PFS) and overall survival (OS) of IMJUDO and durvalumab in combination with platinum-based chemotherapy compared to platinum-based chemotherapy alone. Additional efficacy outcome measures were overall response rate (ORR) and duration of response (DoR). PFS, ORR, and DoR were assessed using Blinded Independent Central Review (BICR) according to RECIST v1.1.

A total of 675 patients were randomized to receive either IMJUDO with durvalumab and platinum-based chemotherapy (n=338) or platinum-based chemotherapy (n=337). The median age was 63 years (range: 27 to 87), 46% of patients age ≥ 65 years, 77% male, 57% White, 34% Asian, 0.3% Native Hawaiian or Other Pacific Islander, 3% American Indian or Alaska Native, 2% Black or African American, 4% Other Race, 79% former or current smoker, 34% ECOG PS 0, and 66% ECOG PS 1. Thirty-six percent had squamous histology, 63% non-squamous histology, 29% PD-L1 expression TC ≥ 50%, 71% PD-L1 expression TC < 50%.

Efficacy results are summarized in Table 10 and Figure 2.

Table 10. Efficacy Results for POSEIDON
 | IMJUDO with durvalumab and platinum-based chemotherapy (n=338) | Platinum-based chemotherapy; (n=337)
OS [PFS/OS results are based on planned analyses which occurred 25/45 months respectively after study initiation.]
Number of deaths (%) | 251 (74) | 285 (85)
Median OS (months) (95% CI) | 14.0; (11.7, 16.1) | 11.7; (10.5, 13.1)
HR (95% CI) | 0.77 (0.65, 0.92)
p-value [2-sided p-values based on log-rank tests stratified by PD-L1, histology and disease stage and compared to a boundary value of 0.00735 for PFS and 0.00797 for OS.] | 0.00304
PFS
Number of events (%) | 238 (70) | 258 (77)
Median PFS (months) (95% CI) | 6.2; (5.0, 6.5) | 4.8; (4.6, 5.8)
HR (95% CI) | 0.72 (0.60, 0.86)
p-value | 0.00031
ORR % (95% CI) [Confirmed responses with 95% Clopper-Pearson confidence intervals.] | 39 (34, 44) | 24 (20, 29)
Median DoR (months); (95% CI) | 9.5; (7.2, NR) | 5.1; (4.4, 6.0)
NR=Not Reached, CI=Confidence Interval

Figure 2. Kaplan-Meier curves of OS in POSEIDON

16 HOW SUPPLIED/STORAGE AND HANDLING

IMJUDO (tremelimumab-actl) injection is a clear to slightly opalescent, colorless to slightly yellow solution supplied in a carton containing one single-dose vial in the following concentrations:

- 25 mg/1.25 mL (20 mg/mL) (NDC 0310-4505-25)
- 300 mg/15 mL (20 mg/mL) (NDC 0310-4535-30)

Store in a refrigerator at 2°C to 8°C (36°F to 46°F) in original carton to protect from light.

Do not freeze. Do not shake.

17 PATIENT COUNSELING INFORMATION

Advise the patient to read the FDA-approved patient labeling (Medication Guide).

Immune-Mediated Adverse Reactions

Inform patients of the risk of immune-mediated adverse reactions that may require corticosteroid treatment and interruption or discontinuation of IMJUDO in combination with durvalumab, including [see Warnings and Precautions (5.1)]:

- Pneumonitis: Advise patients to contact their healthcare provider immediately for any new or worsening cough, chest pain, or shortness of breath.
- Colitis: Advise patients to contact their healthcare provider immediately for diarrhea, blood or mucus in stools, or severe abdominal pain.
- Hepatitis: Advise patients to contact their healthcare provider immediately for jaundice, severe nausea or vomiting, pain on the right side of abdomen, lethargy, or easy bruising or bleeding.
- Endocrinopathies: Advise patients to contact their healthcare provider immediately for signs or symptoms of hypothyroidism, hyperthyroidism, adrenal insufficiency, type 1 diabetes mellitus, or hypophysitis.
- Nephritis: Advise patients to contact their healthcare provider immediately for signs or symptoms of nephritis.
- Dermatological Reactions: Advise patients to contact their healthcare provider immediately for signs or symptoms of severe dermatological reactions.
- Pancreatitis: Advise patients to contact their healthcare provider immediately for signs or symptoms of pancreatitis.
- Other Immune-Mediated Adverse Reactions: Advise patients to contact their healthcare provider immediately for signs or symptoms of aseptic meningitis, immune thrombocytopenia, myocarditis, hemolytic anemia, myositis, uveitis, keratitis, and myasthenia gravis.

Infusion-Related Reactions:

- Advise patients to contact their healthcare provider immediately for signs or symptoms of infusion-related reactions [see Warnings and Precautions (5.2)].

Embryo-Fetal Toxicity:

- Advise females of reproductive potential that IMJUDO can cause harm to a fetus and to inform their healthcare provider of a known or suspected pregnancy [see Warnings and Precautions (5.3) and Use in Specific Populations (8.1, 8.3)].
- Advise females of reproductive potential to use effective contraception during treatment and for 3 months after the last dose of IMJUDO [see Use in Specific Populations (8.3)].

Lactation:

- Advise female patients not to breastfeed while taking IMJUDO and for 3 months after the last dose [see Warnings and Precautions (5.3) and Use in Specific Populations (8.2)].

Manufactured for:

AstraZeneca Pharmaceuticals LP

Wilmington, DE 19850

Manufactured By:

AstraZeneca AB

Södertälje, Sweden SE-15185

US License No. 2059

IMJUDO® is a registered trademark of AstraZeneca group of companies.

©AstraZeneca 2022

MEDICATION GUIDE
IMJUDO® (im-JEW-doh)

(tremelimumab-actl)

injection

What is the most important information I should know about IMJUDO?

IMJUDO is a medicine that may treat certain cancers by working with your immune system.

IMJUDO in combination with durvalumab can cause your immune system to attack normal organs and tissues in any area of your body and can affect the way they work. These problems can sometimes become severe or life-threatening and can lead to death. You can have more than one of these problems at the same time. These problems may happen anytime during treatment or even after your treatment has ended.

Call or see your healthcare provider right away if you develop any new or worsening signs or symptoms, including:

Lung problems.

  - cough

- shortness of breath

- chest pain

Intestinal problems.

- diarrhea (loose stools) or more frequent bowel movements than usual
- stools that are black, tarry, sticky, or have blood or mucus

- severe stomach-area (abdomen) pain or tenderness

Liver problems.

- yellowing of your skin or the whites of your eyes
- severe nausea or vomiting
- pain on the right side of your stomach-area (abdomen)

- dark urine (tea colored)
- bleeding or bruising more easily than normal

Hormone gland problems.

- headaches that will not go away or unusual headaches
- eye sensitivity to light
- eye problems
- rapid heartbeat
- increase sweating
- extreme tiredness
- weight gain or weight loss
- feeling more hungry or thirsty than usual

- urinating more often than usual
- hair loss
- feeling cold
- constipation
- your voice gets deeper
- dizziness or fainting
- changes in mood or behavior, such as decreased sex drive, irritability, or forgetfulness

Kidney problems.

- decrease in your amount of urine
- blood in your urine

- swelling of your ankles
- loss of appetite

Skin problems.

- rash
- itching
- skin blistering or peeling

- painful sores or ulcers in mouth or nose, throat, or genital area
- fever or flu-like symptoms
- swollen lymph nodes

Pancreas problems.

- pain in your upper stomach-area (abdomen)
- severe nausea or vomiting

- loss of appetite

Problems can also happen in other organs and tissues. These are not all of the signs and symptoms of immune system problems that can happen with IMJUDO. Call or see your healthcare provider right away for any new or worsening signs or symptoms, which may include:

- chest pain, irregular heartbeats, shortness of breath or swelling of ankles
- confusion, sleepiness, memory problems, changes in mood or behavior, stiff neck, balance problems
- tingling, numbness or weakness of the arms or legs
- double vision, blurry vision, sensitivity to light, eye pain, changes in eye sight
- persistent or severe muscle pain or weakness, muscle cramps, joint pain, joint stiffness or swelling
- low red blood cells, bruising

Infusion reactions that can sometimes be severe or life-threatening. Signs and symptoms of infusion reactions may include:

- chills or shaking
- itching or rash
- flushing
- shortness of breath or wheezing

- dizziness
- feel like passing out
- fever
- back or neck pain

Getting medical treatment right away may help keep these problems from becoming more serious.

Your healthcare provider will check you for these problems during your treatment with IMJUDO. Your healthcare provider may treat you with corticosteroid or hormone replacement medicines. Your healthcare provider may also need to delay or completely stop treatment with IMJUDO, if you have severe side effects.

What is IMJUDO?

IMJUDO is a prescription medicine used to treat adults with:

- a type of liver cancer called unresectable hepatocellular carcinoma (uHCC). IMJUDO may be used in combination with durvalumab when your uHCC cannot be removed by surgery.
- a type of lung cancer called non-small cell lung cancer (NSCLC). IMJUDO may be used in combination with durvalumab and chemotherapy that contains platinum when your NSCLC:
- has spread to other part of your body (metastatic), and
- your tumor does not have an abnormal “EGFR” or “ALK” gene.

It is not known if IMJUDO is safe and effective in children.

Before you receive IMJUDO, tell your healthcare provider about all of your medical conditions, including if you:

- have immune system problems such as Crohn's disease, ulcerative colitis, or lupus
- have a condition that affects your nervous system, such as myasthenia gravis or Guillain-Barré syndrome
- are pregnant or plan to become pregnant. IMJUDO can harm your unborn baby.

Females who are able to become pregnant

  - Your healthcare provider should do a pregnancy test before you start treatment with IMJUDO.
  - You should use an effective method of birth control during your treatment and for 3 months after your last dose of IMJUDO. Talk to your healthcare provider about birth control methods that you can use during this time.
  - Tell your healthcare provider right away if you become pregnant or think you may be pregnant during treatment with IMJUDO.
- are breastfeeding or plan to breastfeed. It is not known if IMJUDO passes into your breast milk. Do not breastfeed during treatment and for 3 months after your last dose of IMJUDO.

Tell your healthcare provider about all the medicines you take, including prescription and over-the-counter medicines, vitamins, and herbal supplements.

How will I receive IMJUDO?

- Your healthcare provider will determine your treatment schedule and cycles of treatment.
- Your healthcare provider will give you IMJUDO into your vein through an intravenous (IV) line over 60 minutes.
- For the treatment of uHCC:
  - On the same day you receive IMJUDO, you will receive durvalumab through an intravenous (IV) line over 60 minutes.
  - IMJUDO is given to you as a single dose.
  - You will then receive durvalumab every 4 weeks
- For the treatment of NSCLC:
  - On the same day you receive IMJUDO, you will receive durvalumab followed by platinum-containing chemotherapy. You will receive combination chemotherapy every 3 weeks for four cycles (Cycle 1 to 4).
  - You will then receive durvalumab for one cycle (Cycle 5), and then IMJUDO in combination with durvalumab for one cycle only (Cycle 6).
  - You will then receive durvalumab every 4 weeks.
  - Your healthcare provider will decide if you will also receive additional chemotherapy with each cycle.
- Your healthcare provider will test your blood to check you for certain side effects.
- If you miss your appointment, call your healthcare provider as soon as possible to reschedule your appointment.

What are the possible side effects of IMJUDO?

IMJUDO can cause serious side effects, including:

See “What is the most important information I should know about IMJUDO?”

The most common side effects of IMJUDO when used in combination with durvalumab in adults with uHCC include:

- rash
- diarrhea
- feeling tired

- itchiness
- muscle or bone pain
- stomach area (abdominal) pain

The most common side effects of IMJUDO when used in combination with durvalumab and platinum-containing chemotherapy in adults with metastatic NSCLC include:

- nausea
- feeling tired or weak
- muscle or bone pain

- decreased appetite
- rash
- diarrhea

Tell your healthcare provider if you have any side effect that bothers you or that does not go away.

These are not all the possible side effects of IMJUDO. Ask your healthcare provider or pharmacist for more information.

Call your doctor for medical advice about side effects. You may report side effects to FDA at 1-800-FDA-1088.

General information about the safe and effective use of IMJUDO.

Medicines are sometimes prescribed for purposes other than those listed in a Medication Guide. If you would like more information about IMJUDO, talk with your healthcare provider. You can ask your healthcare provider for information about IMJUDO that is written for health professionals.

What are the ingredients in IMJUDO?

Active ingredient: tremelimumab-actl

Inactive ingredients: edetate disodium, histidine, L-histidine hydrochloride monohydrate, polysorbate 80, trehalose, and Water for Injection, USP.

Manufactured for: AstraZeneca Pharmaceuticals LP, Wilmington, DE 19850

Manufactured by: AstraZeneca AB, Södertälje, Sweden SE-15185

US License No. 2059

IMJUDO® is a registered trademark of AstraZeneca group of companies.

For more information, call 1-800-236-9933 or go to www.IMJUDO.com

© AstraZeneca 2024

This Medication Guide has been approved by the U.S. Food and Drug Administration. Revised: 01/2024

PACKAGE/LABEL PRINCIPAL DISPLAY PANEL

NDC 0310-4535-30 Rx only

IMJUDO® 300 mg/15 mL

(tremelimumab-actl) (20 mg/mL)

Injection

For Intravenous Infusion After Dilution

Single-dose vial. Discard unused portion.

Attention Pharmacist:

Dispense the accompanying Medication Guide

to each patient.

AstraZeneca

PACKAGE/LABEL PRINCIPAL DISPLAY PANEL

NDC 0310-4505-25 Rx only

IMJUDO® 25 mg/1.25 mL

(tremelimumab-actl) (20 mg/mL)

Injection

For Intravenous Infusion After Dilution

Single-dose vial. Discard unused portion.

Attention Pharmacist:

Dispense the accompanying Medication Guide

to each patient.

AstraZeneca